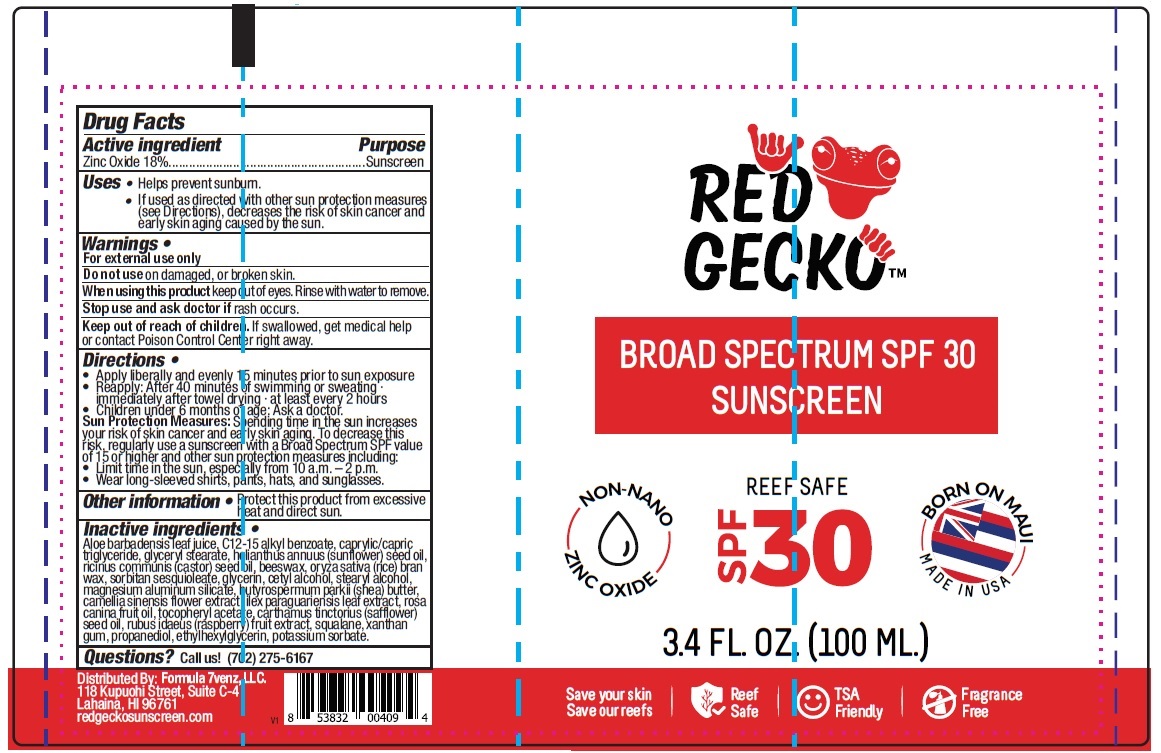 DRUG LABEL: Red Gecko Broad Spectrum SPF 30 Sunscreen
NDC: 82086-002 | Form: LOTION
Manufacturer: Formula 7venz L.L.C.
Category: otc | Type: HUMAN OTC DRUG LABEL
Date: 20251216

ACTIVE INGREDIENTS: ZINC OXIDE 18 g/100 mL
INACTIVE INGREDIENTS: ALOE VERA LEAF; ALKYL (C12-15) BENZOATE; MEDIUM-CHAIN TRIGLYCERIDES; GLYCERYL MONOSTEARATE; SUNFLOWER OIL; CASTOR OIL; YELLOW WAX; RICE BRAN; SORBITAN SESQUIOLEATE; GLYCERIN; CETYL ALCOHOL; STEARYL ALCOHOL; MAGNESIUM ALUMINUM SILICATE; SHEA BUTTER; CAMELLIA SINENSIS FLOWER; ILEX PARAGUARIENSIS LEAF; ROSA CANINA FRUIT OIL; .ALPHA.-TOCOPHEROL ACETATE; SAFFLOWER OIL; RASPBERRY; SQUALANE; XANTHAN GUM; PROPANEDIOL; ETHYLHEXYLGLYCERIN; POTASSIUM SORBATE

RED GECKO™ BROAD SPECTRUM SPF 30 SUNSCREEN

Active ingredient

Zinc Oxide 18%

Purpose

Sunscreen

Uses

• Helps prevent sunburn.

• If used as directed with other sun protection measures (see Directions), decreases the risk of cancer and early skin aging caused by the sun.

Warnings

For external use only

Do not use on damaged, or broken skin.

When using this product keep out of eyes. Rinse with water to remove.

Stop use and ask doctor if rash occurs.

Keep out of reach of children. If swallowed, get medical help or contact Poison Control Center right away.

Directions

• Apply liberally and evenly 15 minutes prior to sun exposure

• Reapply: After 40 minutes of swimming or sweating · immediately after towel drying · at least every 2 hours

• Children under 6 months of age: Ask a doctor.

Sun Protection Measures : Spending time in the sun increases your risk of skin cancer and early skin aging. To decrease this risk, regularly

use a sunscreen with a Broad Spectrum SPF value of 15 or higher and other sun protection measures including:

• Limit time in the sun, especially from 10 a.m. - 2 p.m.

• Wear long-sleeved shirts, pants, hats, and sunglasses.

Other information

• Protect this product from excessive heat and direct sun.

Inactive ingredients

Aloe barbadensis leaf juice, C12-15 alkyl benzoate, caprylic/capric triglyceride, glyceryl stearate, helianthus annuus (sunflower) seed

oil, ricinus communis (castor) seed oil, beeswax, oryza sativa (rice) bran wax, sorbitan sesquioleate, glycerin, cetyl alcohol, stearyl

alcohol, magnesium aluminum silicate, butyrospermum parkii (shea) butter, camellia sinensis flower extract, ilex paraguariensis

leaf extract, rosa canina fruit oil, tocopheryl acetate, carthamus tinctorius (safflower) seed oil, rubus idaeus (raspberry) fruit

extract, squalane, xanthan gum, propanediol, ethylhexylglycerin, potassium sorbate.

Questions?

Call us! (702) 275-6167

REEF SAFE

NON-NANO

BORN ON MAUI

MADE IN USA

Save your skin

Save our reefs

TSA Friendly

Fragrance Free

Distributed by: Formula 7venz, LLC.

118 Kupuohi Street Suite C-4

Lahaina, HI 96761

redgeckosunscreen.com